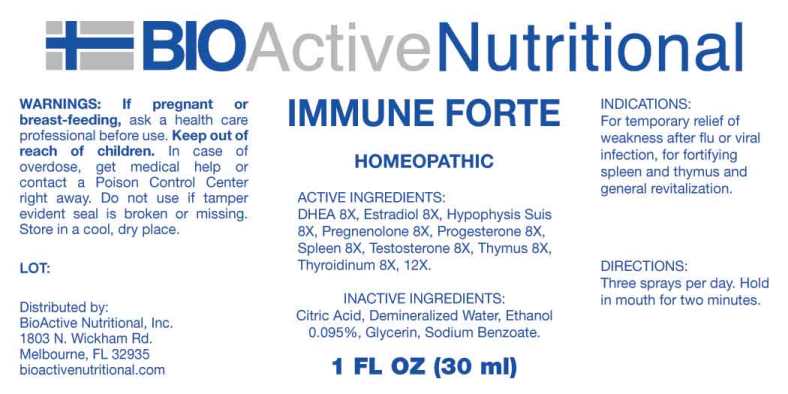 DRUG LABEL: Immune Forte
NDC: 43857-0166 | Form: LIQUID
Manufacturer: BioActive Nutritional, Inc.
Category: homeopathic | Type: HUMAN OTC DRUG LABEL
Date: 20240829
DEA Schedule: CIII

ACTIVE INGREDIENTS: PRASTERONE 8 [hp_X]/1 mL; ESTRADIOL 8 [hp_X]/1 mL; SUS SCROFA PITUITARY GLAND 8 [hp_X]/1 mL; PREGNENOLONE 8 [hp_X]/1 mL; PROGESTERONE 8 [hp_X]/1 mL; BOS TAURUS SPLEEN 8 [hp_X]/1 mL; TESTOSTERONE 8 [hp_X]/1 mL; SUS SCROFA THYMUS 8 [hp_X]/1 mL; THYROID 8 [hp_X]/1 mL
INACTIVE INGREDIENTS: CITRIC ACID MONOHYDRATE; GLYCERIN; SODIUM BENZOATE; WATER; ALCOHOL

DRUG FACTS:

ACTIVE INGREDIENTS:

Dehydroepiandrosterone (DHEA) 8X, Estradiol 8X, Hypophysis Suis 8X, Pregnenolone 8X, Progesterone 8X, Spleen (Bovine) 8X, Testosterone 8X, Thymus (Suis) 8X, Thyroidinum (Suis) 8X, 12X.

INDICATIONS:

For temporary relief of weakness after flu or viral infection, for fortifying spleen and thymus and general revitalization.

WARNINGS:

If pregnant or breast-feeding, ask a health care professional before use.

Keep out of reach of children. In case of overdose, get medical help or contact a Poison Control Center right away.

Do not use if tamper evident seal is broken or missing.

Store in a cool, dry place.

Keep out of reach of children. In case of overdose, get medical help or contact a Poison Control Center right away.

DIRECTIONS:

Three sprays per day. Hold in mouth for two minutes.

INDICATIONS:

For temporary relief of weakness after flu or viral infection, for fortifying spleen and thymus and general revitalization.

INACTIVE INGREDIENTS:

Citric Acid, Demineralized Water, Ethanol 0.095%, Glycerin, Sodium Benzoate.

QUESTIONS:

Distributed by:
BioActive Nutritional, Inc.
1803 N. Wickham Rd.
Melbourne, FL 32935
bioactivenutritional.com

PACKAGE LABEL DISPLAY:

BIOActive Nutritional

IMMUNE FORTE

HOMEOPATHIC

1 FL OZ (30 ml)